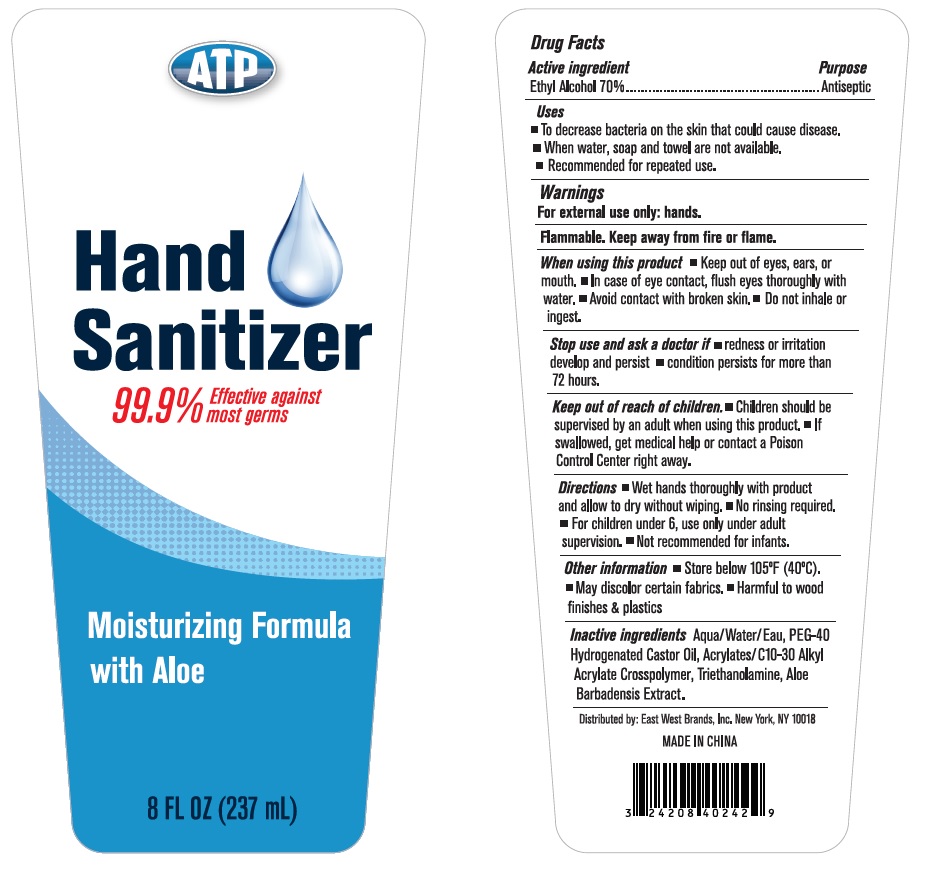 DRUG LABEL: ATP HAND SANITIZER
NDC: 73960-001 | Form: GEL
Manufacturer: East West Brands Inc.
Category: otc | Type: HUMAN OTC DRUG LABEL
Date: 20200421

ACTIVE INGREDIENTS: ALCOHOL 70 mL/100 mL
INACTIVE INGREDIENTS: WATER; POLYOXYL 40 HYDROGENATED CASTOR OIL; CARBOMER INTERPOLYMER TYPE A (ALLYL SUCROSE CROSSLINKED); TROLAMINE; ALOE VERA LEAF

ATP Hand Sanitizer

Active ingredient

Ethyl Alcohol 70%

Purpose

Antiseptic

Uses

▪ To decrease bacteria on the skin that could cause disease.

▪ When water, soap and towel are not available.

▪ Recommended for repeated use.

Warnings

For external use only: hands.

Flammable. Keep away from fire or flame.

When using this product ▪ Keep out of eyes, ears, or mouth. ▪ In case of eye contact, flush eyes thoroughly with water. ▪ Avoid contact with broken skin. ▪ Do not inhale or ingest.

Stop use and ask a doctor if ▪ redness or irritation develop and persist ▪ condition persists for more than 72 hours.

Keep out of reach of children. ▪ Children should be supervised by an adult when using this product. ▪ If swallowed, get medical help or contact a Poison Control Center right away.

DOSAGE AND ADMINISTRATION

Directions ▪ Wet hands thoroughly with product and allow to dry without wiping. ▪ No rinsing required. ▪ For children under 6, use only under adult supervision. ▪ Not recommended for infants.

Other information ▪ Store below 105°F (40°C). ▪ May discolor certain fabrics. ▪ Harmful to wood finishes & plastics

INACTIVE INGREDIENT

Inactive ingredients Aqua/Water/Eau, PEG-40 Hydrogenated Castor Oil, Acrylates/C10-30 Alkyl Acrylate Crosspolymer, Triethanolamine, Aloe Barbadensis Extract.

99.9% Effective against most germs

Moisturizing Formula with Aloe

Distributed by: East West Brands, Inc. New York, NY 10018

MADE IN CHINA